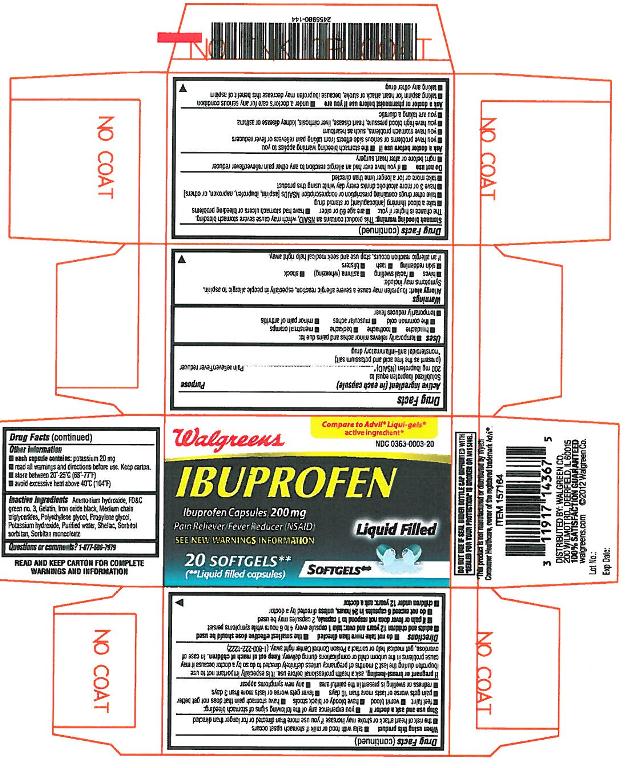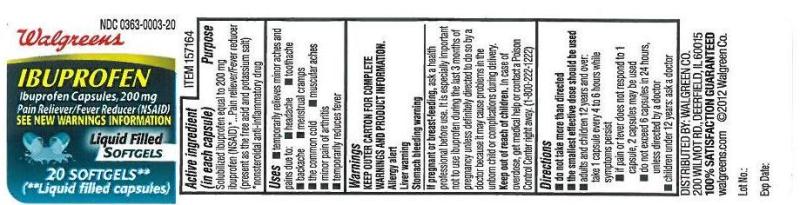 DRUG LABEL: IBUPROFEN
                        
NDC: 0363-0003 | Form: CAPSULE, LIQUID FILLED
Manufacturer: Walgreen Company
Category: otc | Type: Human OTC Drug Label
Date: 20120522

ACTIVE INGREDIENTS: IBUPROFEN 200 mg/1 1
INACTIVE INGREDIENTS: AMMONIA; FD&C GREEN NO. 3; GELATIN; SORBITOL; WATER; SHELLAC; SORBITAN MONOOLEATE; POLYETHYLENE GLYCOL; PROPYLENE GLYCOL; FERROSOFERRIC OXIDE; MEDIUM-CHAIN TRIGLYCERIDES; POTASSIUM HYDROXIDE

Active ingredient(s)

(in each capsule)
Solubilized Ibuprofen equal to

200 mg ibuprofen (NSAID)*

(present as the free acid and potassium salt)

* nonsteroidal anti-inflammatory drug

Purpose

Pain reliever/Fever reducer

Use(s)

- temporarily relieves minor aches and pain due to :
  - headache
  - toothache
  - backache
  - menstrual cramps
  - the common cold
  - muscular aches
  - minor pain of arthritis
- temporarily reduces fever

Warnings

Allergy alerts: Ibuprofen may cause a severe allergic reaction, especially in people allergic to aspirin. Symptoms may include:

- hives
- facial swelling
- asthma (wheezing)
- shock
- skin reddening
- rash
- blisters

If an allergic reaction occurs, stop use and seek medical help right away.

Stomach bleeding warning: This product contains an NSAID, which may cause severe stomach bleeding. The chance is higher if you:

- are age 60 or older
- have had stomach ulcers or bleeding problems
- take a blood thinning (anticoagulant) or steroid drug
- take other drugs containing prescription or nonprescription NSAIDs [aspirin, ibuprofen, naproxen, or others]
- have 3 or more alcoholic drinks every day while using this product
- take more or for a longer time than directed

Do not use

- if you have ever had an allergic reaction to any other pain reliever/fever reducer
- right before or after heart surgery

Ask a doctor before use if

- stomach bleeding warning applies to you
- you have problems or serious side effects from taking pain relievers or fever reducers
- you have a history of stomach problems, such as heartburn
- you have high blood pressure, heart disease, liver cirrhosis, kidney disease, or asthma
- you are taking a diuretic

Ask a doctor or pharmacist before use if

- under a doctor’s care for any serious condition
- taking aspirin for heart attack or stroke, because Ibuprofen may decrease this benefit of aspirin
- taking any other drug

When using this product

- take with food or milk if stomach upset occurs
- the risk of heart attack or stroke may increase if you use more than directed or for longer than directed

Stop use and ask doctor if

- you experience any of following signs of stomach bleeding:
  - feel faint
  - vomit blood
  - have bloody or black stools
  - have stomach pain that dose not get better
- pain gets worse or lasts more than 10 days
- fever gets worse or lasts more than 3 days
- redness or swelling is present in painful area
- any new symptoms appear

Pregnancy/Breastfeeding

ask a health professional before use. It is especially important not to use Ibuprofen during the last 3 months of pregnancy unless definitely directed to do so by a doctor because it may cause a problems in the unborn child or complications during delivery.

Keep out of reach of children

In case of overdose, get medical help or contact a Poison ControlCenter right away.(1-800-222-1222)

Directions

- do not take more than directed
- the smallest effective dose should be used
- adults and children 12 years and over: take 1 capsule every 4 to 6 hours while symptoms persist
- if pain or fever dose not respond to 1 capsule, 2 capsules may be used
- do not exceed 6 capsules in 24 hours, unless directed by a doctor
- children under 12 years: ask a doctor

Other information

- each capsule contains: potassium 20 mg
- read all warnings and directions before use.
- store at 20-25 oC (68-77 oF)
- avoid excessive heat above 40 oC (104 oF)

Inactive ingredients

Ammonium hydroxide, FD&C green no.3, Gelatin, Iron oxide black, Medium chain triglycerides, Polyethylene glycol, Propylene glycol, Potassium hydroxide, Purified water, Shellac, Sorbitol, Sorbitan monooleate

Principal Display Panel

20ct_Carton
20ct_Label

Questions or Comments? 1-877-586-7979